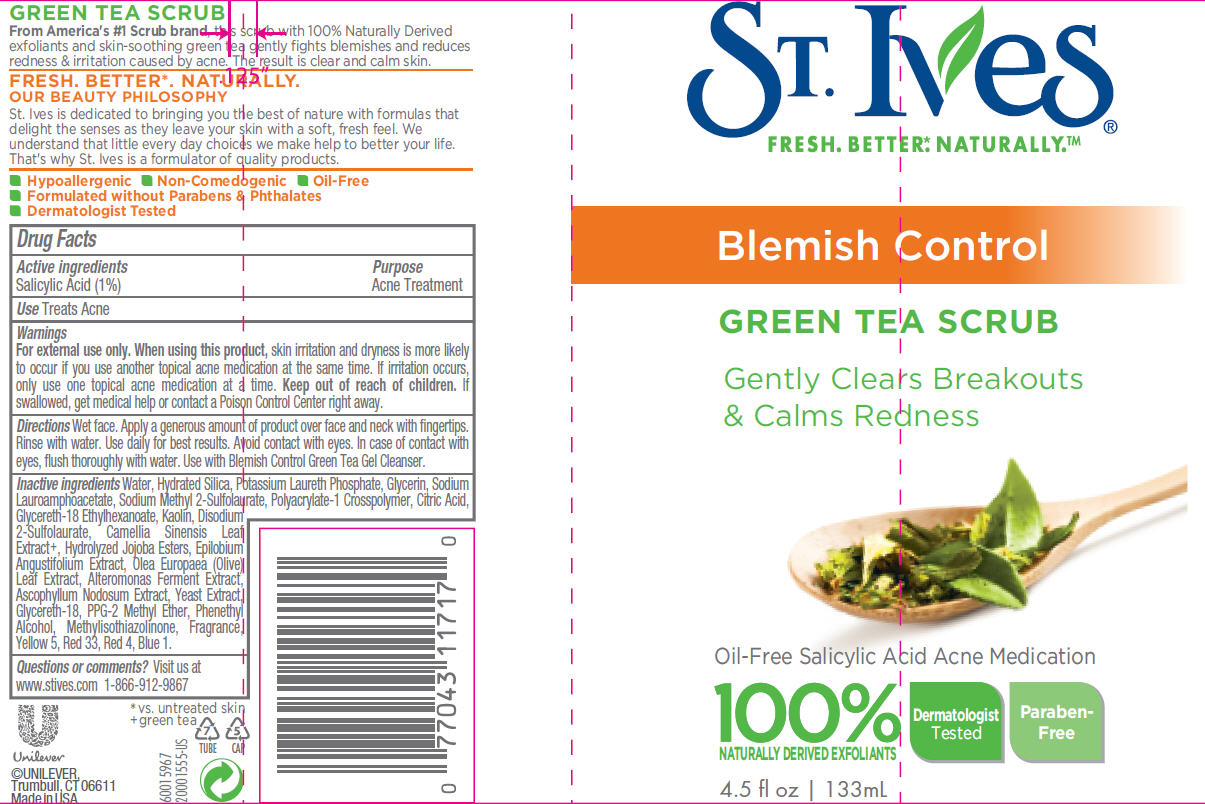 DRUG LABEL: St. Ives
NDC: 64942-1247 | Form: EMULSION
Manufacturer: CONOPCO Inc. d/b/a Unilever
Category: otc | Type: HUMAN OTC DRUG LABEL
Date: 20120308

ACTIVE INGREDIENTS: Salicylic Acid 0.01 mL/1 mL
INACTIVE INGREDIENTS: WATER; HYDRATED SILICA; GLYCERIN; SODIUM LAUROAMPHOACETATE; SODIUM METHYL 2-SULFOLAURATE; CITRIC ACID MONOHYDRATE; GLYCERETH-18 ETHYLHEXANOATE; DISODIUM 2-SULFOLAURATE; KAOLIN; HYDROLYZED JOJOBA ESTERS (ACID FORM); GLYCERETH-18; PPG-2 METHYL ETHER; PHENYLETHYL ALCOHOL; OLEA EUROPAEA LEAF; ASCOPHYLLUM NODOSUM; METHYLISOTHIAZOLINONE; YEAST; GREEN TEA LEAF; FD&C BLUE NO. 1; FD&C YELLOW NO. 5; D&C RED NO. 33; FD&C RED NO. 4

St. Ives Green Tea Scrub

Active ingredient
Salicylic Acid (1%)

Purpose
Acne Treatment

Use
Treats Acne

Warnings
For external use only.

When using this product, skin irritation and dryness is more likely to occur if you use another topical acne medication at the same time. If irritation occurs, only use one topical acne medication at a time.

Keep out of reach of children. If swallowed, get medical help or contact a Poison Control Center right away.

Directions
Wet face. Apply a generous amount of product over face and neck with fingertips. Rinse with water. Use twice daily for best results. Avoid contact with eyes. In case of contact with eyes, flush thoroughly with water. Use with Blemish Control Green Tea Gel Cleanser.

Inactive ingredients

Water (Aqua, Eau)

Hydrated Silica

Potassium Laureth Phosphate

Glycerin

Sodium Lauroamphoacetate

Sodium Methyl 2-Sulfolaurate

Polyacrylate-1 Crosspolymer

Citric Acid

Glycereth-18 Ethylhexanoate

Disodium 2-Sulfolaurate

Kaolin

Salicylic Acid

Hydrolyzed Jojoba Esters

Parfum (Fragrance)

Glycereth-18

Phenethyl Alcohol

PPG-2 Methyl Ether

Epilobium Angustifolium Extract

Olea Europaea (Olive) Leaf Extract

Alteromonas Ferment Extract

Ascophyllum Nodosum Extract

Methylisothiazolinone

Yellow 5 (CI 19140)

CI 14700 (Red 4)

CI 17200 (Red 33)

CI 42090 (Blue 1)

Camellia Sinensis Leaf Extract

Yeast Extract

Questions or comments?
Visit us at www.stives.com 1-866-912-9867

PACKAGE LABEL

PDP